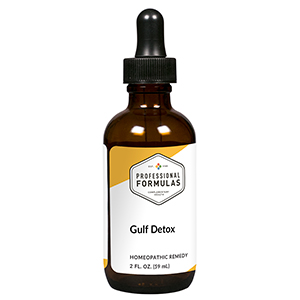 DRUG LABEL: Gulf Detox
NDC: 63083-6038 | Form: LIQUID
Manufacturer: Professional Complementary Health Formulas
Category: homeopathic | Type: HUMAN OTC DRUG LABEL
Date: 20190815

ACTIVE INGREDIENTS: ARCTIUM LAPPA ROOT OIL 3 [hp_X]/59 mL; TARAXACUM OFFICINALE 3 [hp_X]/59 mL; TRIFOLIUM PRATENSE FLOWER 3 [hp_X]/59 mL; CHLOROPHYLL 6 [hp_X]/59 mL; ANTHRACENE 30 [hp_X]/59 mL; BENZENE 30 [hp_X]/59 mL; XYLENE (MIXED ISOMERS) 30 [hp_X]/59 mL; PROPYLENE GLYCOL 12 [hp_X]/59 mL; LIQUID PETROLEUM 12 [hp_X]/59 mL; POLYCYCLIC AROMATIC HYDROCARBONS 30 [hp_X]/59 mL
INACTIVE INGREDIENTS: ALCOHOL; WATER

X38

ACTIVE INGREDIENTS

Arctium lappa 3X
Taraxacum officinale 3X
Trifolium pratense 3X
Chlorophyllum 6X
Anthracene 30X
Benzene 30X
Xylene 30X
Dispersant isode combination 12X, 30X, 60X, 100X
Gulf water 12X, 30X, 60X, 100X
Petroleum 12X, 30X, 60X, 100X
Hydrocarbons (various) 30X, 60X, 100X

QUESTIONS

Professional Formulas

PO Box 2034 Lake Oswego, OR 97035

INDICATIONS

For the temporary relief of cough, wheezing, eye, nose, or throat irritation, watery or itchy eyes, occasional headache, nausea, sore throat, fatigue, or tiredness due to sensitivity to or exposure to contaminants found in oil spills.*

PURPOSE

*Claims based on traditional homeopathic practice, not accepted medical evidence. Not FDA evaluated.

WARNINGS

Consult a doctor if condition worsens or symptoms persist. Keep out of the reach of children. In case of overdose, get medical help or contact a poison control center right away. If pregnant or breastfeeding, ask a healthcare professional before use.

Keep out of the reach of children.

PREGNANCY OR BREAST FEEDING

If pregnant or breastfeeding, ask a healthcare professional before use.

DIRECTIONS

Place drops under tongue 30 minutes before/after meals. Adults and children 12 years and over: Take 10 drops up to 3 times per day. Consult a physician for use in children under 12 years of age.

OTHER INFORMATION

Tamper resistant. If seal is broken, do not use. After opening, close container tightly and store at room temperature away from heat.

INACTIVE INGREDIENTS

20% ethanol, purified water.

LABEL

Est 1985

Professional Formulas

Complementary Health

Gulf Detox

Homeopathic Remedy

2 FL. OZ. (59 mL)